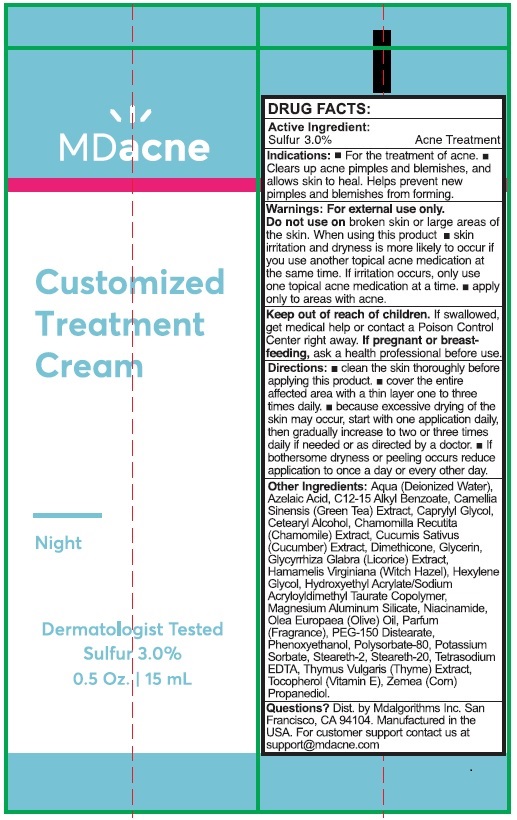 DRUG LABEL: MDacne Customized Cream (Sulfur)
NDC: 71804-400 | Form: CREAM
Manufacturer: MDalgorithms Inc.
Category: otc | Type: HUMAN OTC DRUG LABEL
Date: 20220209

ACTIVE INGREDIENTS: SULFUR 3 mg/100 mL
INACTIVE INGREDIENTS: WATER; AZELAIC ACID; ALKYL (C12-15) BENZOATE; CAMELLIA SINENSIS FLOWER; CAPRYLYL GLYCOL; CETOSTEARYL ALCOHOL; CHAMOMILE; CUCUMBER; DIMETHICONE; GLYCERIN; GLYCYRRHIZA GLABRA; WITCH HAZEL; HEXYLENE GLYCOL; HYDROXYETHYL ACRYLATE/SODIUM ACRYLOYLDIMETHYL TAURATE COPOLYMER (100000 MPA.S AT 1.5%); MAGNESIUM ALUMINUM SILICATE; NIACINAMIDE; OLIVE OIL; PEG-150 DISTEARATE; PHENOXYETHANOL; POLYSORBATE 80; POTASSIUM SORBATE; STEARETH-2; STEARETH-20; EDETATE SODIUM; THYME; .ALPHA.-TOCOPHEROL; CORN

DRUG FACTS:

Active Ingredient:

Sulfur 3.0%

PURPOSE

Acne Treatment

Indications: ■ For the treatment of Acne. ■

Clears up acne pimples and blemishes, and

allows skin to heal. Helps prevent new

pimples and blemishes from forming.

Warnings For external use only
Do not useon broken skin or large areas of
the skin. When using this product ■ skin
irritation and dryness is more likely to occur if
you use another topical acne medication at
the same time. If irritation occurs, only use
one acne medication at one time. ■ apply
only to areas with acne.

KEEP OUT OF REACH OF CHILDREN

Keep out of the reach of children. If swallowed,
get medical help or contact a Poison Control Center right away.

If pregnant or breast feeding, ask

a health professional before use.

DOSAGE AND ADMINISTRATION

Directions: ■ clean the skin thoroughly before
applying this product. ■ cover the entire
affected area with a thin layer one to three
times daily ■ Because excessive drying of the
skin may occur, start with one application daily,
then gradually increase to two or three times daily if
needed or directed by a doctor. ■ if
bothersome dryness or peeling occurs reduce
application to once a day or every other day.

INACTIVE INGREDIENT

Other Ingredients: Aqua (Deionized Water),
Azelaic Acid, C12-15 Alkyl Benzoate, Camellia
Sinensis (Green Tea) Extract, Caprylyl Glycol,
Cetearyl Alcohol, Chamomilla Recutita
(Chamomile) Extract, Cucumis Sativus
(Cucumber) Extract, Dimethicone, Glycerin,
Glycyrrhiza Glabra (Licorice) Extract,
Hamamelis Virginiana (Witch Hazel), Hexylene
Glycol, Hydroxyethyl Acrylate/Sodium
Acryloyldimethyl Taurate Copolymer,
Magnesium Aluminum Silicate, Niacinamide,
Olea Europaea (Olive) Oil, Parfum
(Fragrance), PEG-150 Distearate,
Phenoxyethanol, Polysorbate-80, Potassium
Sorbate, Steareth-2, Steareth-20, Tetrasodium
EDTA, Thymus Vulgaris (Thyme) Extract,
Tocopherol (Vitamin E), Zemea (Corn)
Propanediol.

Questions? Dist. by Mdalgorithms Inc. San

Francisco, CA 94104. Manufactured in the

USA. For customer support contact us at

support@mdacne.com

Package Label

MDacne

Customized

Treatment

Cream

Night

Dermatologist Tested

Sulfur 3.0%

0.5 Oz | 15 mL

res